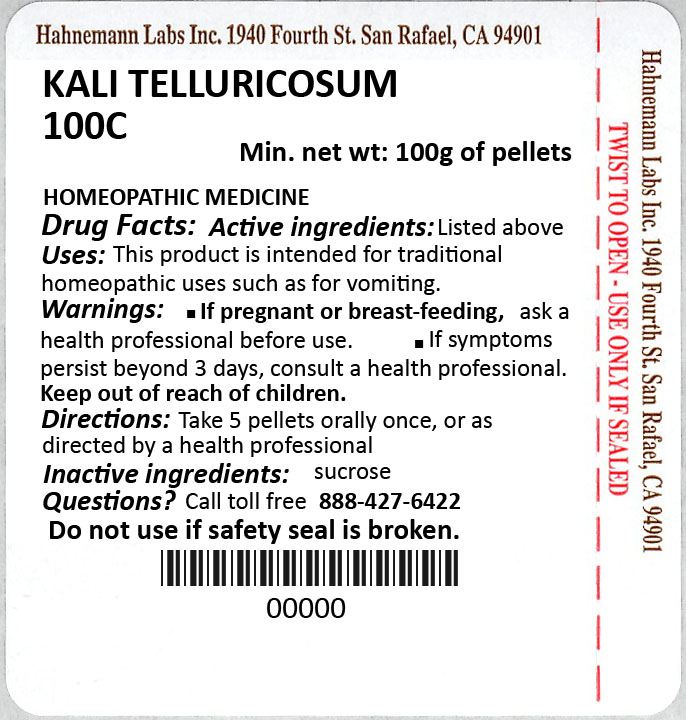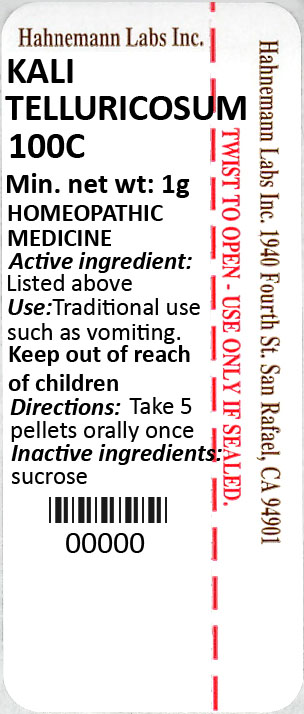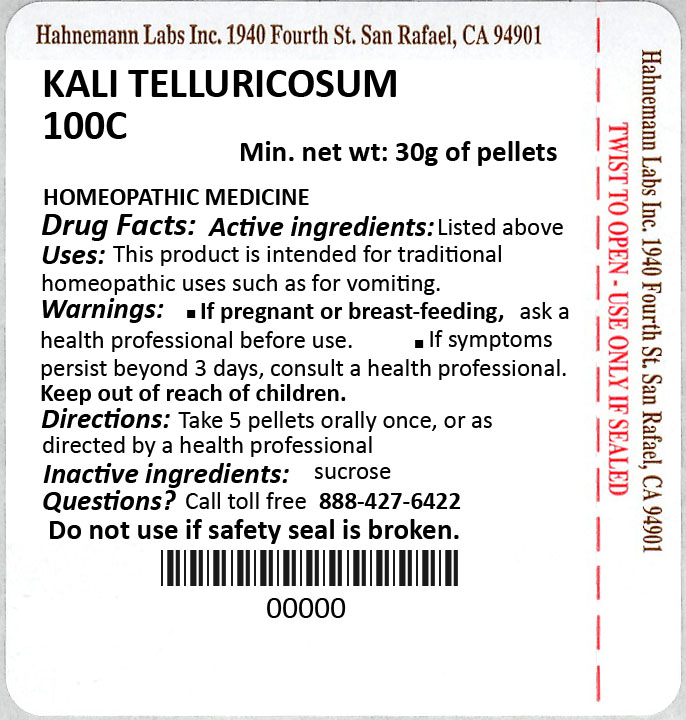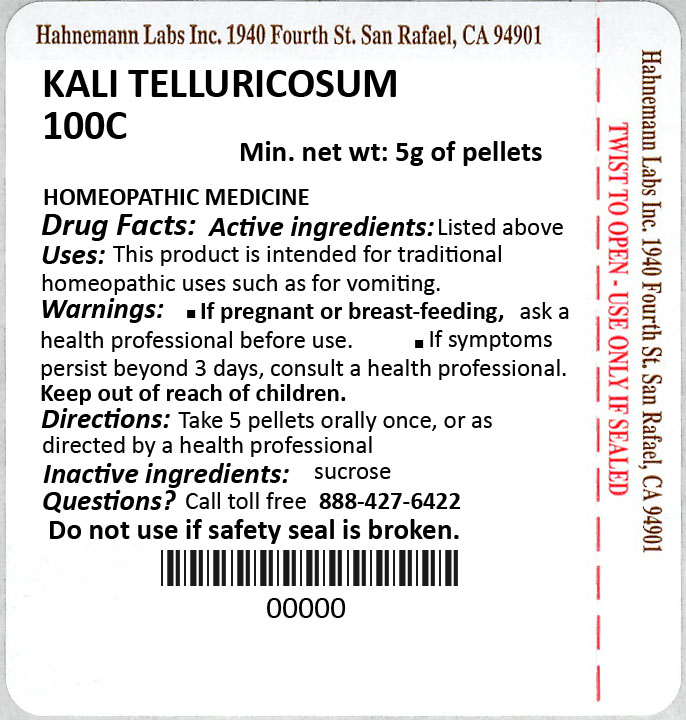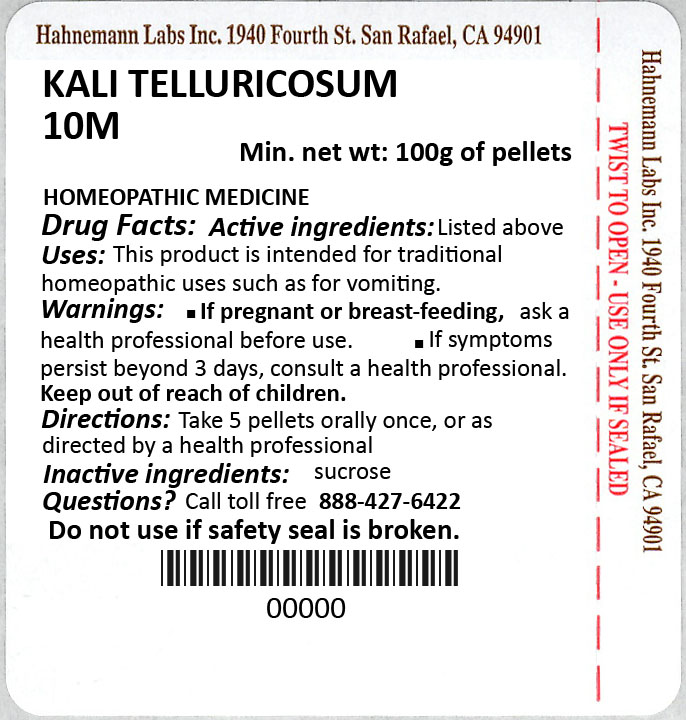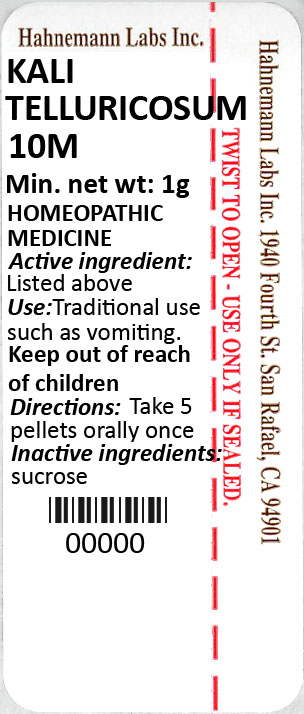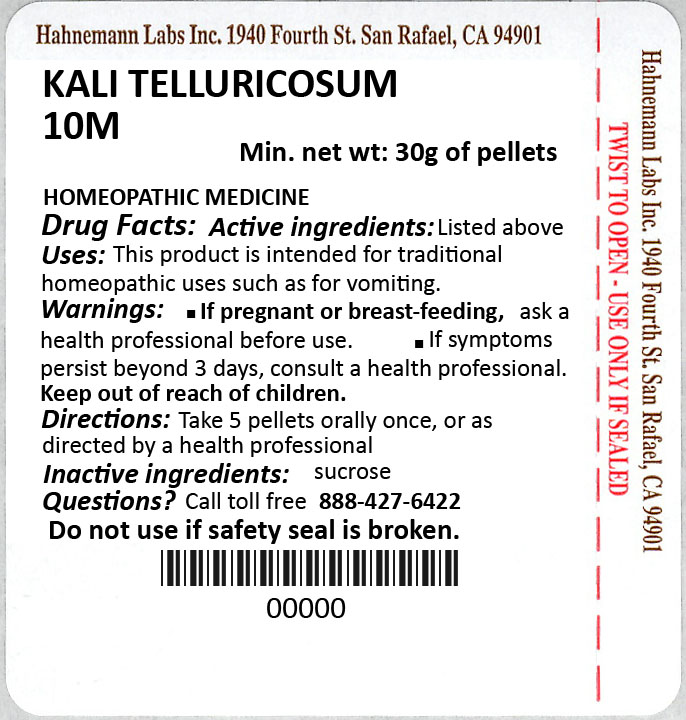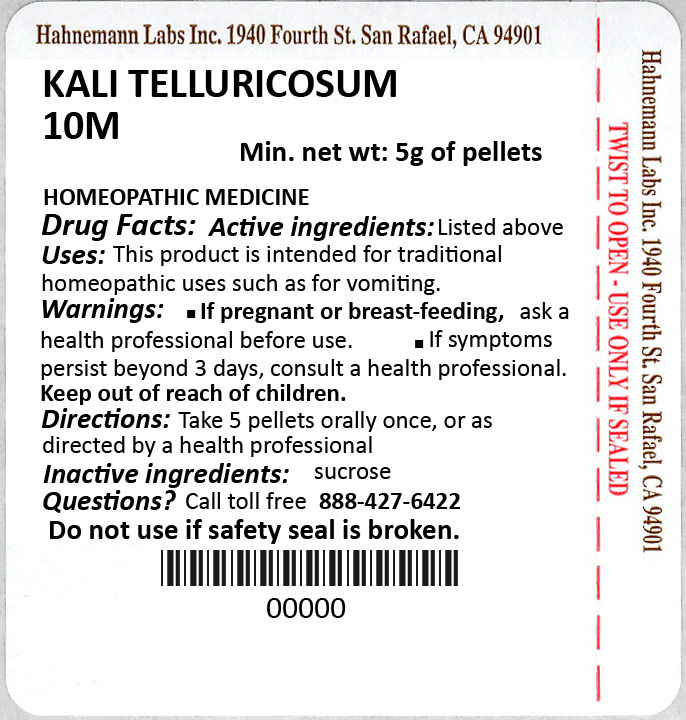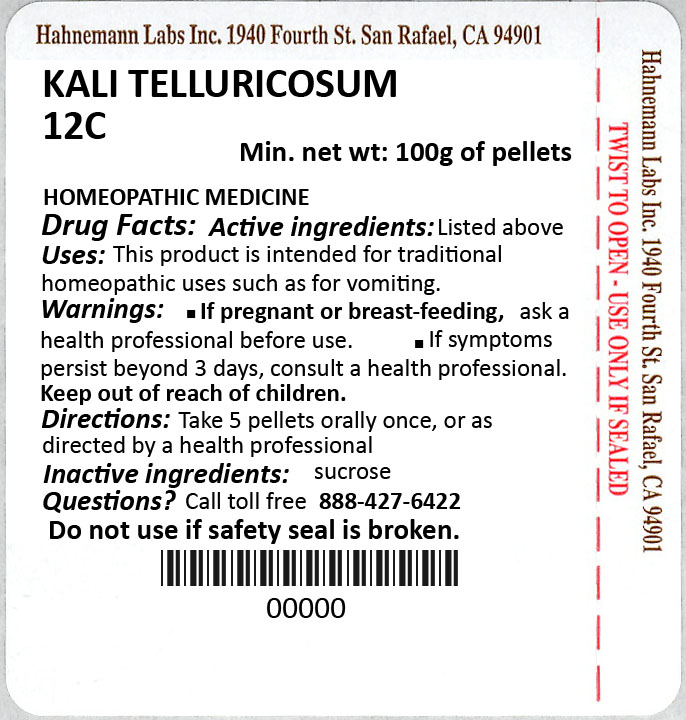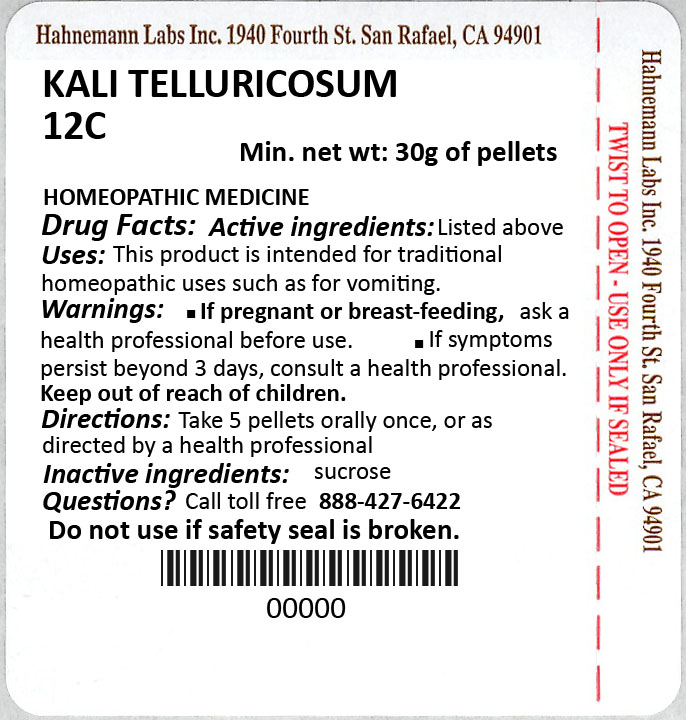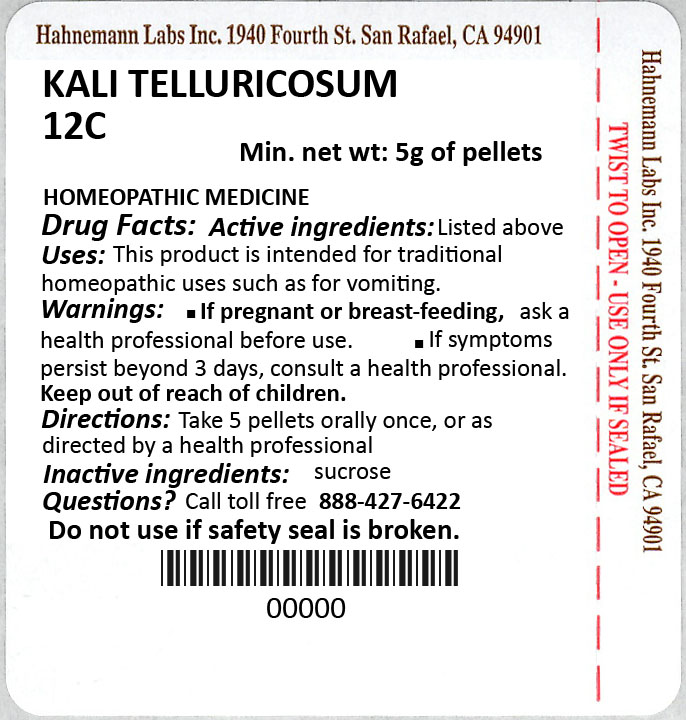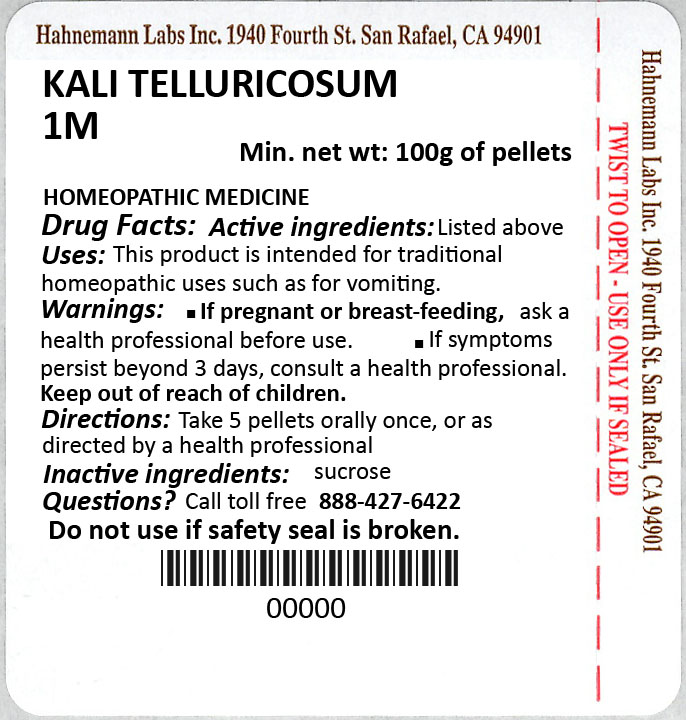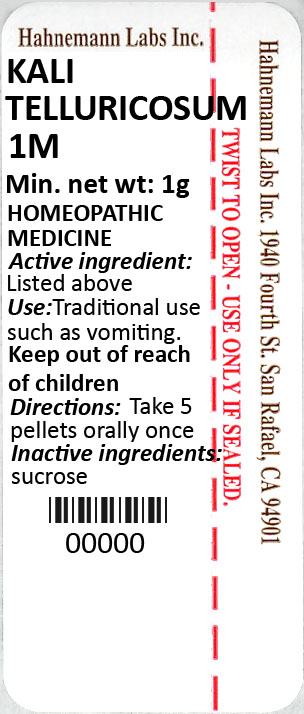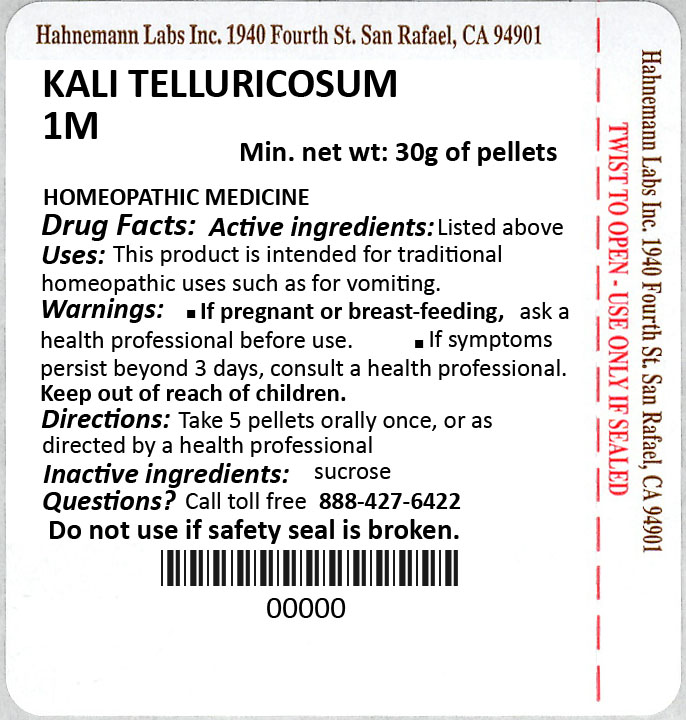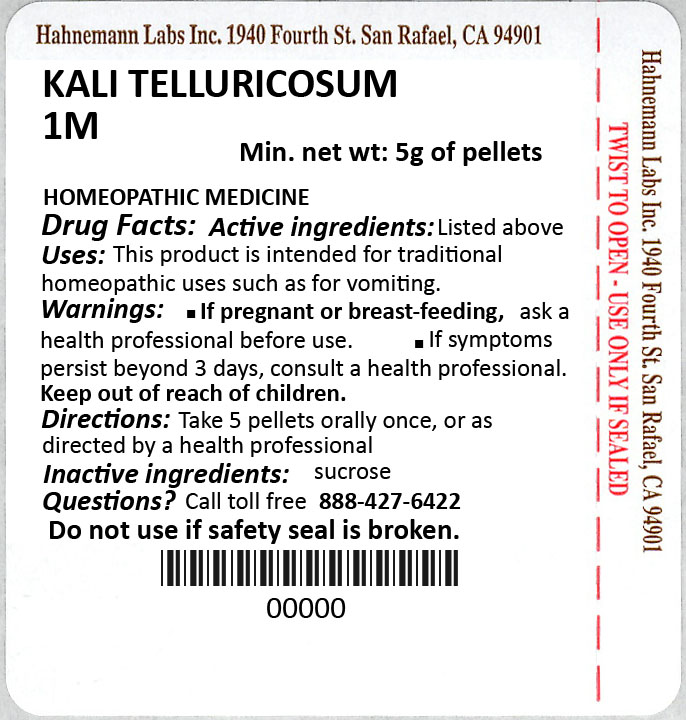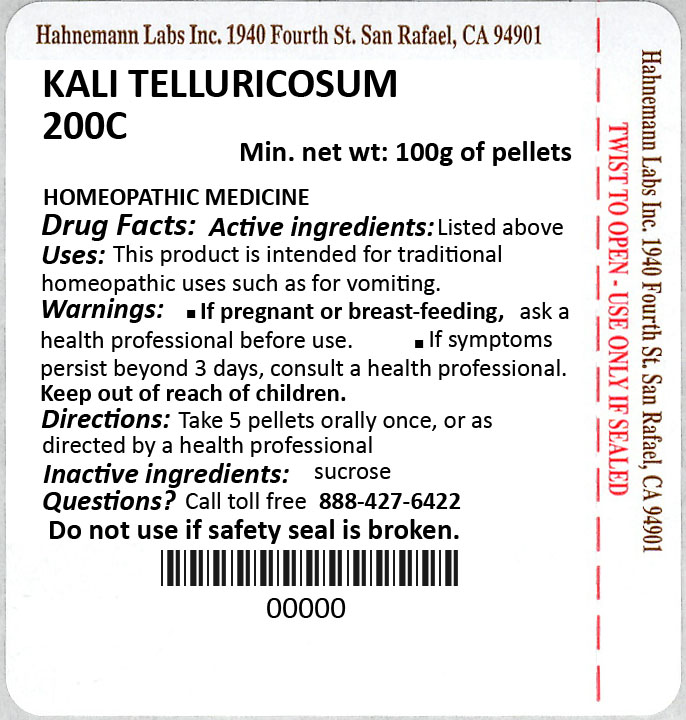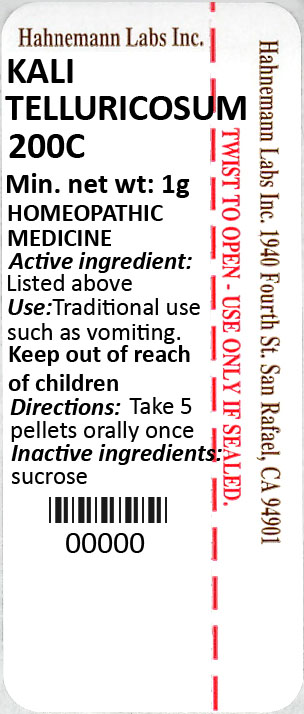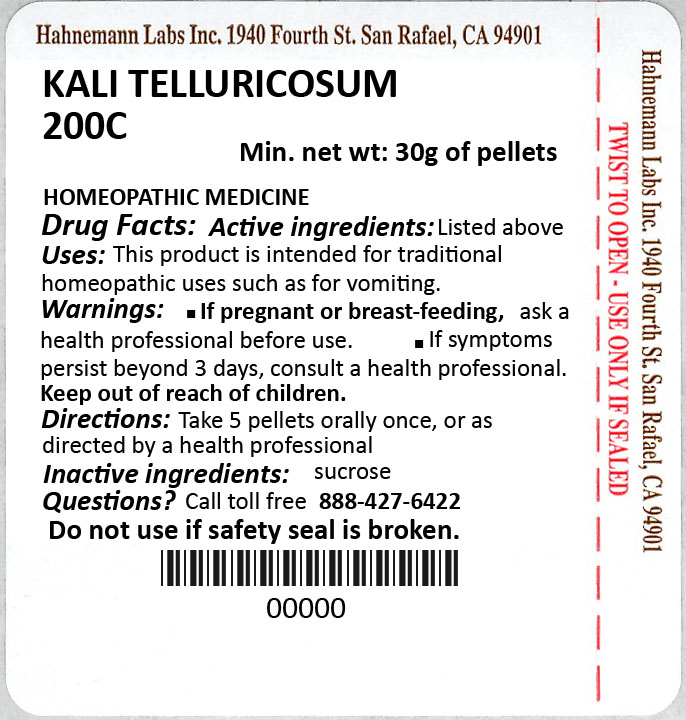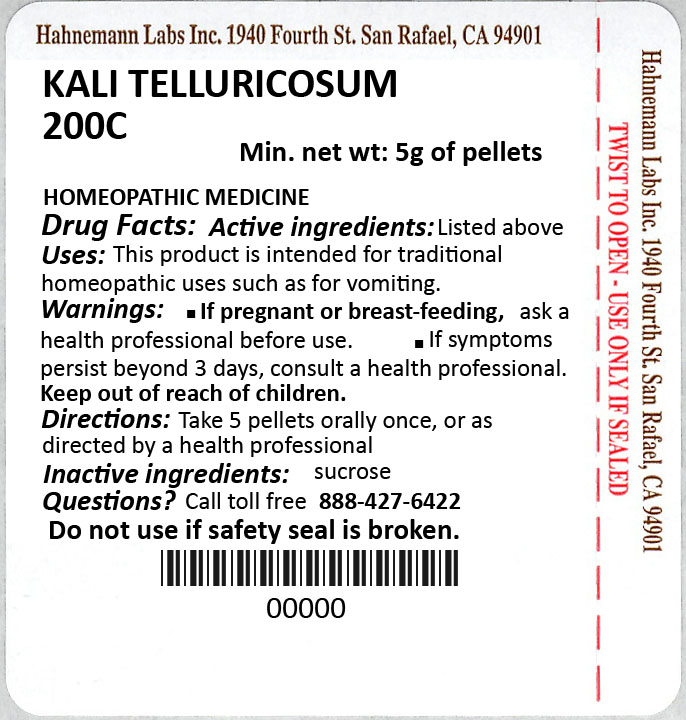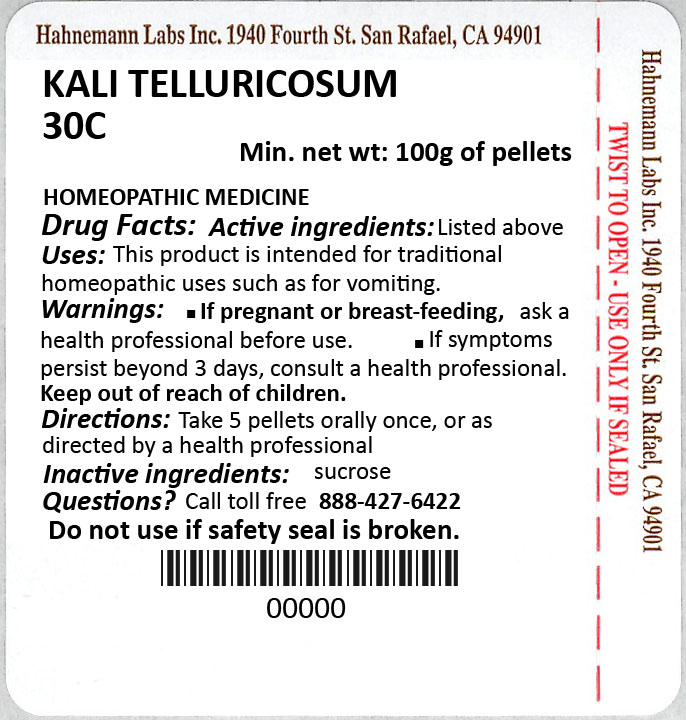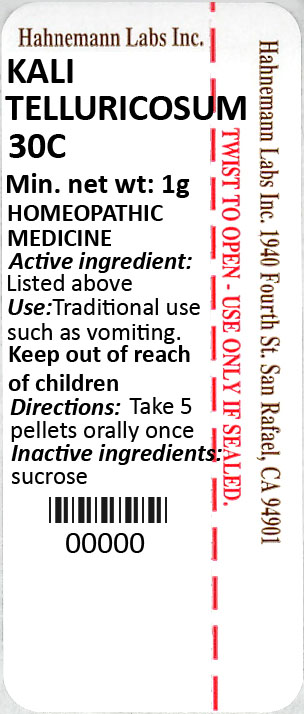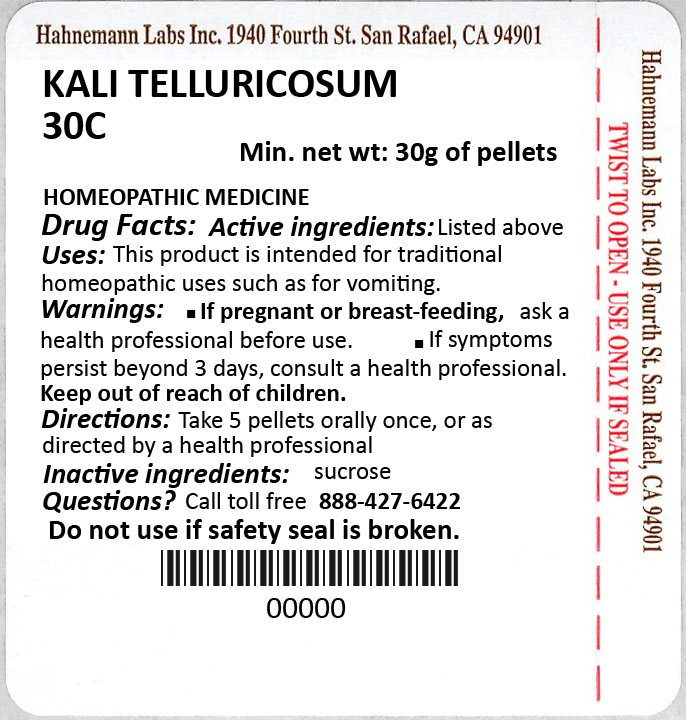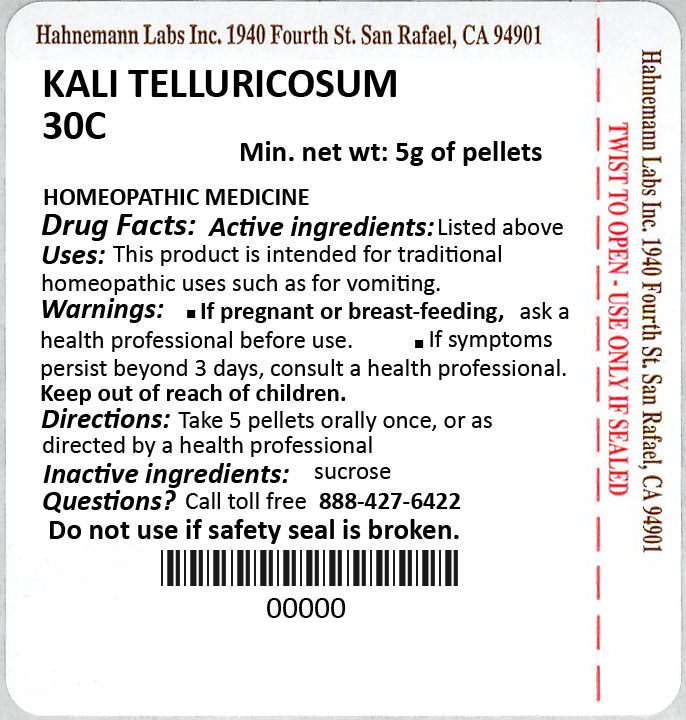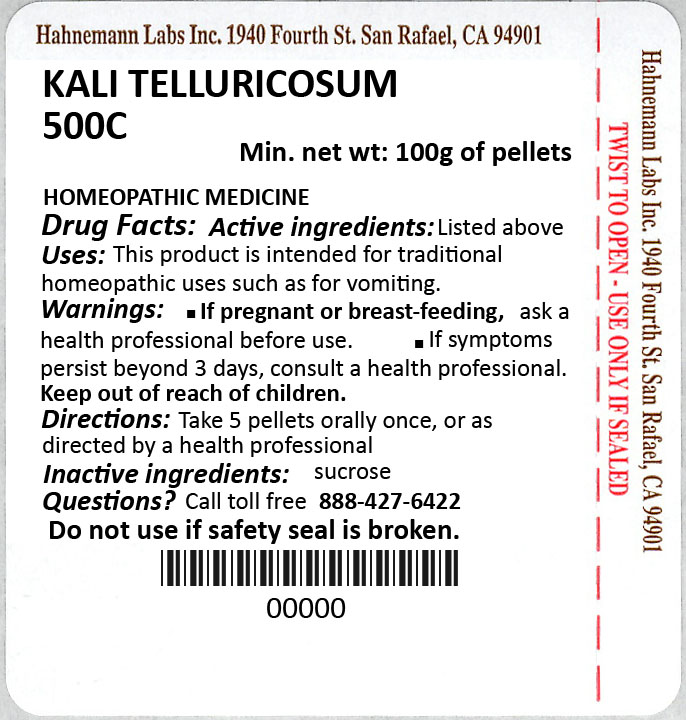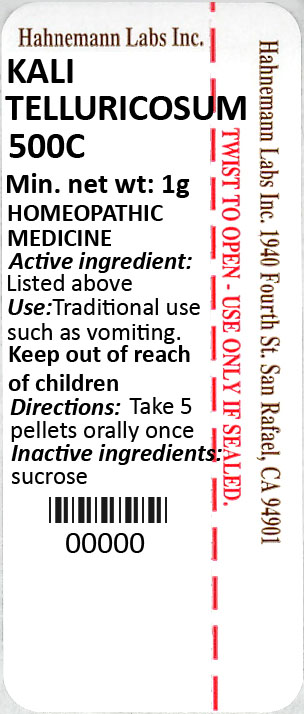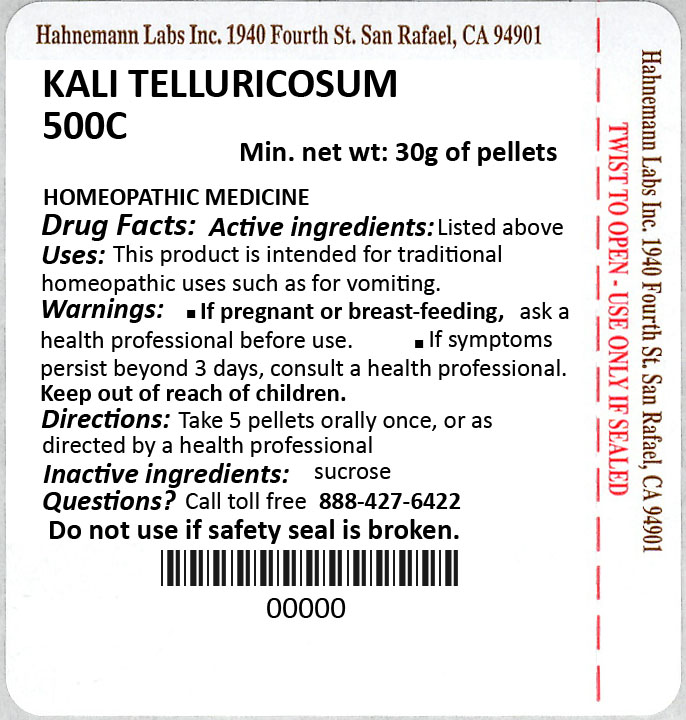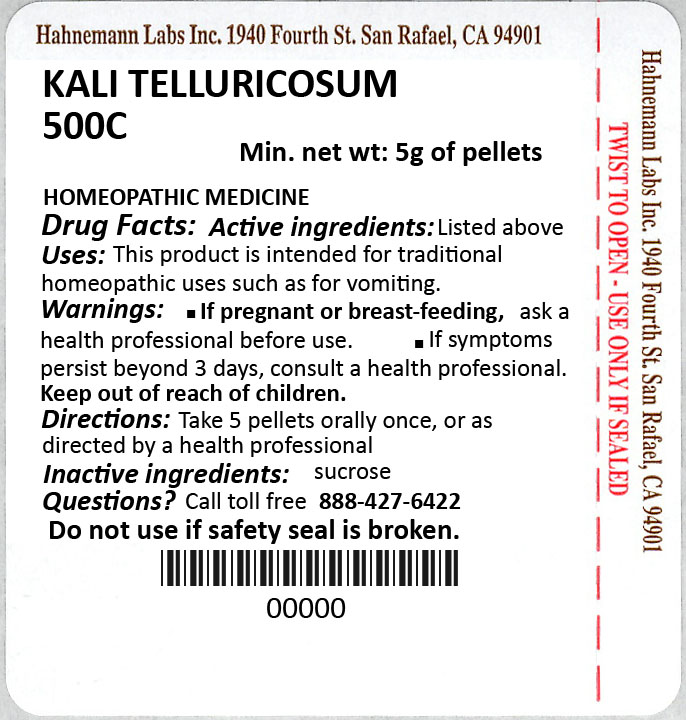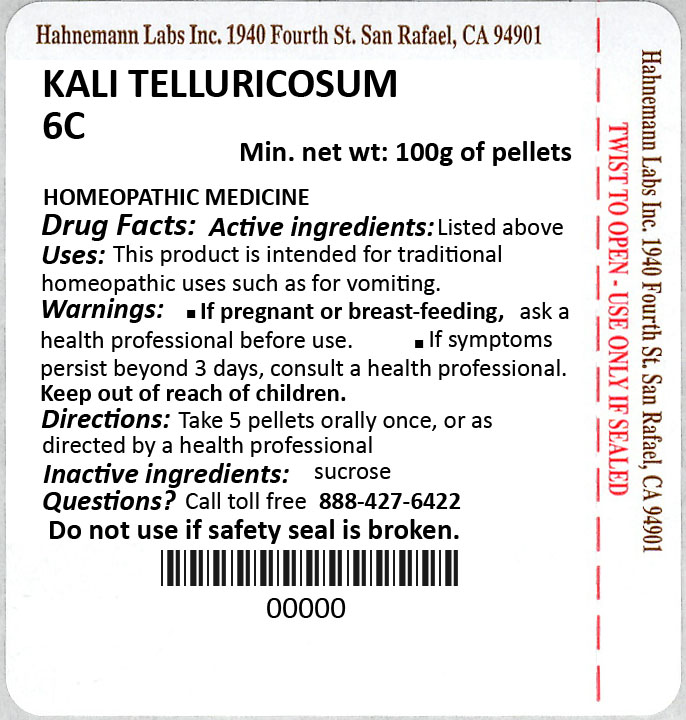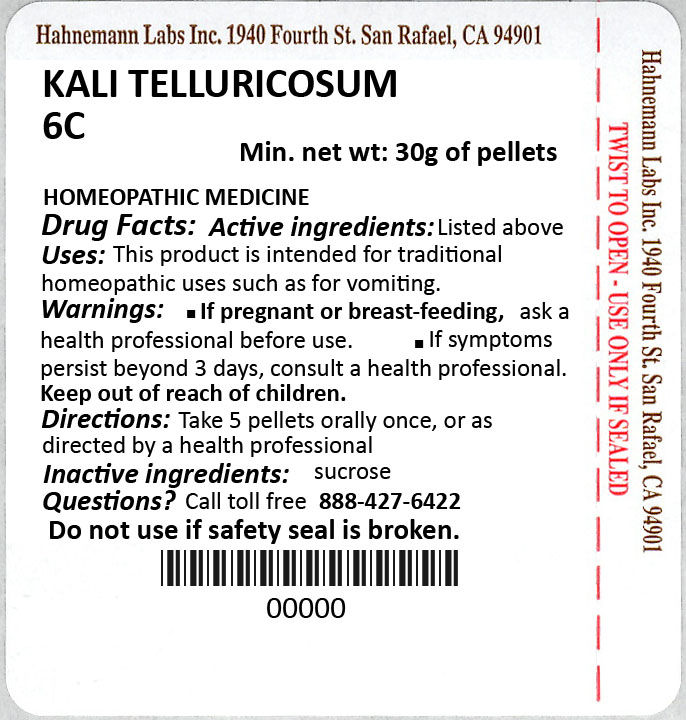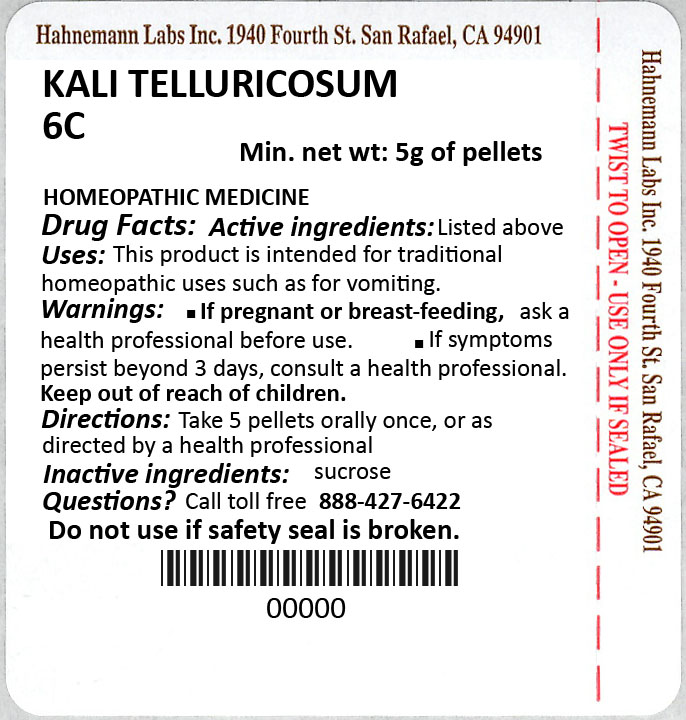 DRUG LABEL: Kali Telluricosum
NDC: 37662-3336 | Form: PELLET
Manufacturer: Hahnemann Laboratories, INC.
Category: homeopathic | Type: HUMAN OTC DRUG LABEL
Date: 20230608

ACTIVE INGREDIENTS: POTASSIUM TELLURITE 12 [hp_C]/1 1
INACTIVE INGREDIENTS: SUCROSE

PACKAGE LABEL

`